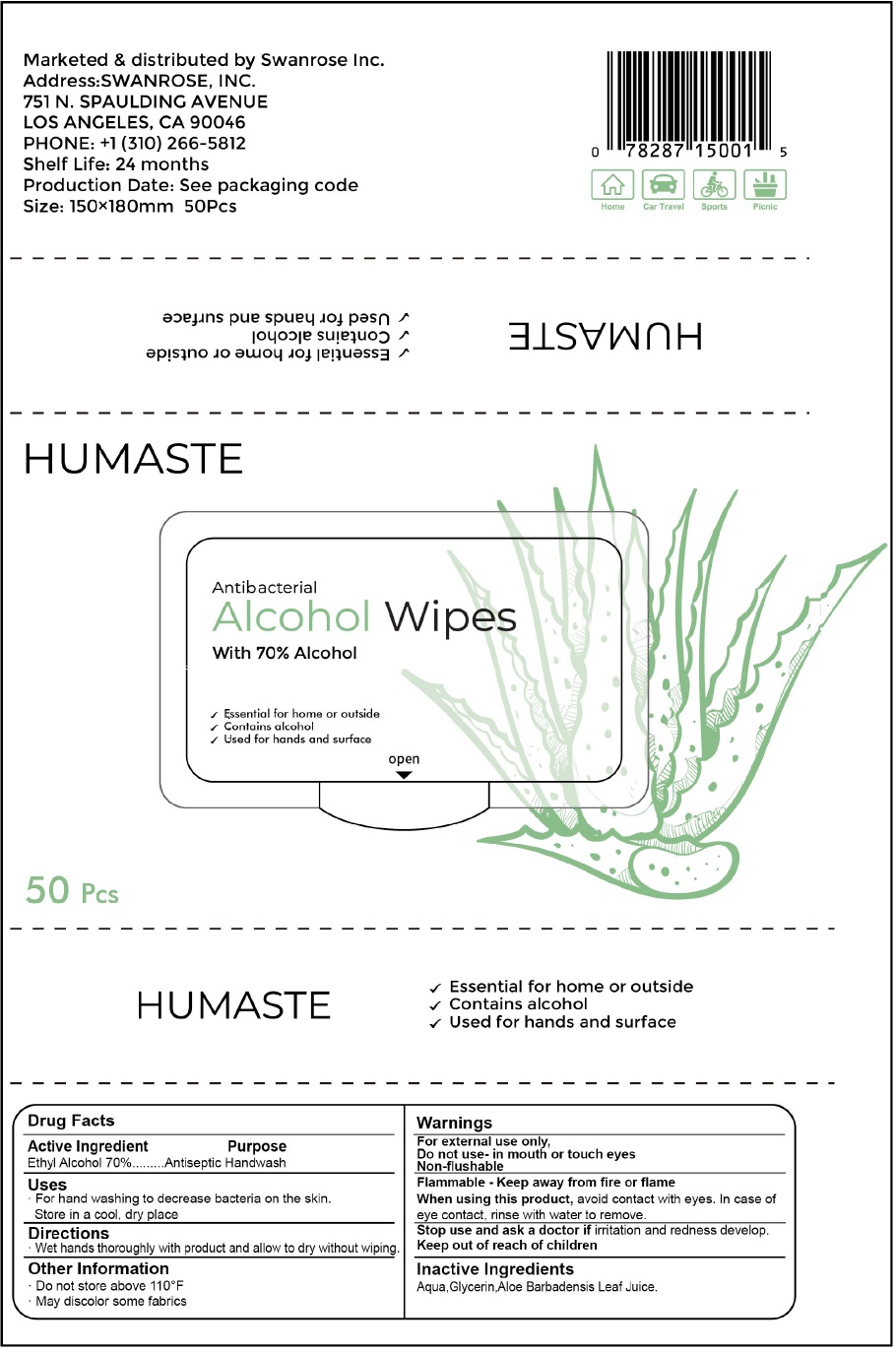 DRUG LABEL: HUMASTE Antibacterial Alcohol Wipes
NDC: 78287-150 | Form: CLOTH
Manufacturer: Swanrose, Inc.
Category: otc | Type: HUMAN OTC DRUG LABEL
Date: 20200710

ACTIVE INGREDIENTS: ALCOHOL 70 mL/100 mL
INACTIVE INGREDIENTS: WATER; GLYCERIN; ALOE VERA LEAF

HUMASTE Antibacterial Alcohol Wipes

Active Ingredient

Ethyl Alcohol 70%

Purpose

Antiseptic Handwash

Uses

· For hand washing to decrease bacteria on the skin.

Store in a cool, dry place

Directions

· Wet hands thoroughly with product and allow to dry without wiping.

Other Information

· Do not store above 110°F

· May discolor some fabrics

Warnings

For external use only,

Do not use- in mouth or touch eyes

Non-flushable

Flammable - Keep away from fire or flame

When using this product, avoid contact with eyes. In case of eye contact, rinse with water to remove.

Stop use and ask a doctor if irritation and redness develop.

Keep out of reach of children

Inactive Ingredients

Aqua,Glycerin,Aloe Barbadensis Leaf Juice.

With 70% Alcohol

√ Essential for home or outside

√ Contains alcohol

√ Used for hands and surface

Marketed & distributed by Swanrose Inc.

Address:SWANROSE, INC.

751 N. SPAULDING AVENUE

LOS ANGELES, CA 90046

PHONE: +1 (310) 266-5812

Shelf Life: 24 months